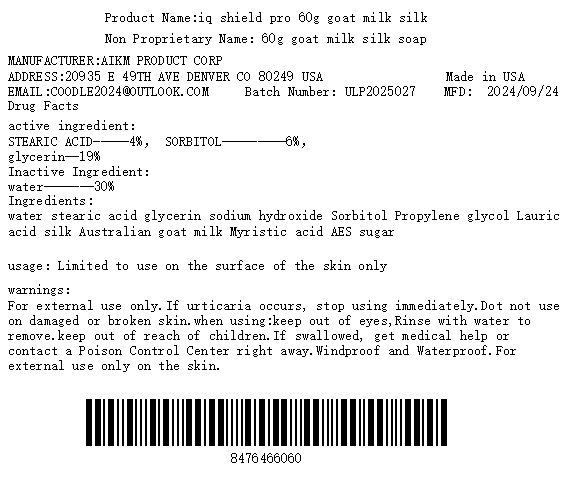 DRUG LABEL: iq shield pro 60g goat milk silk
NDC: 84764-660 | Form: SOAP
Manufacturer: AIKM Product Corp
Category: otc | Type: HUMAN OTC DRUG LABEL
Date: 20250108

ACTIVE INGREDIENTS: STEARIC ACID 40 mg/1 g; GLYCERIN 190 mg/1 g; SORBITOL 60 mg/1 g
INACTIVE INGREDIENTS: WATER 300 mg/1 g

active ingredient

niacinamide-----1% ，Sorbitol---6%，stearic acid---17%

Purpose

relieve pain

usage

Limited to use on the surface of the skin only

warnings

For external use only

stop

rash occurs

do not use

on damaged or broken skin

when using

keep out of eyes. Rinse with water to remove.

keep out of reach of children

If swallowed, get medical help or contact a Poison Control Center right away.

storage

Windproof and Waterproof

For external use only on the skin

INACTIVE INGREDIENT

water-------30%

Use according to the instructions or doctor's advice

RECENT MAJOR CHANGES

stop using